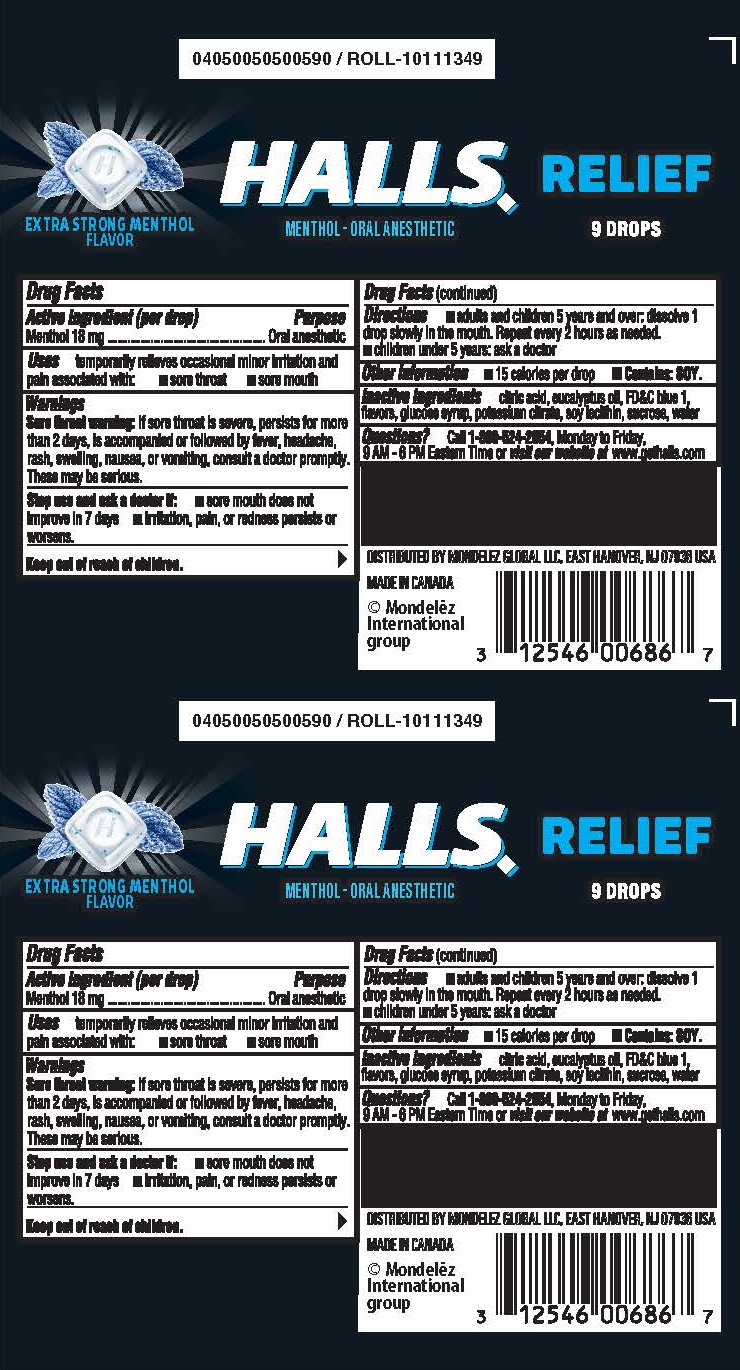 DRUG LABEL: HALLS
NDC: 12546-722 | Form: LOZENGE
Manufacturer: Mondelez Global LLC
Category: otc | Type: HUMAN OTC DRUG LABEL
Date: 20250708

ACTIVE INGREDIENTS: MENTHOL 18 mg/1 1
INACTIVE INGREDIENTS: WATER; CORN SYRUP; SUCROSE; EUCALYPTUS OIL; FD&C BLUE NO. 1; ANHYDROUS CITRIC ACID; POTASSIUM CITRATE; LECITHIN, SOYBEAN

Halls Extra Strong Stick

Active Ingredient

<(per drop) Menthol 18 mg>

Purpose

<Oral Anesthetic>

Uses

Temporarily relieves occasional minor irritation and pain associated with:

- sore mouth
- sore throat

Warnings

<Sore throat warning: if sore throat is severe, persists for more than 2 days, is accompanied or followed by fever, headache, rash, swelling, nausea, or vomiting, consult a doctor promptly. These may be serious.>

Stop use and ask a doctor if:

- sore mouth does not improve in 7 days
- irritation, pain, or redness persists or worsens

Directions

- adults and children 5 years and over: dissolve 1 drop slowly in the mouth. Repeat every 2 hours as needed
- children under 5 years: ask a doctor

Other information

- 15 Calories per drop
- CONTAINS: SOY.

Inactive ingredients

<citric acid, eucalyptus oil, FD&C blue 1, flavors, glucose syrup, potassium citrate, soy lecithin, sucrose, water>

Questions

<Call 1-800-524-2854, Monday to Friday, 9 AM - 6 PM Eastern Time or visit our website at www.gethalls.com>